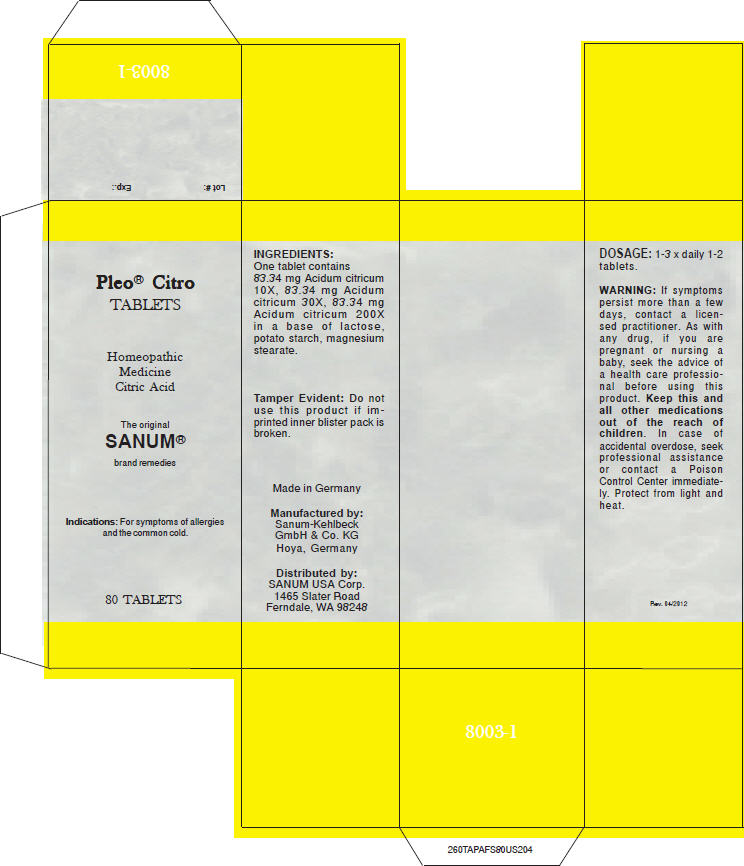 DRUG LABEL: Pleo Citro
NDC: 60681-8003 | Form: TABLET
Manufacturer: Sanum-Kehlbeck GmbH & Co. KG
Category: homeopathic | Type: HUMAN OTC DRUG LABEL
Date: 20120626

ACTIVE INGREDIENTS: CITRIC ACID MONOHYDRATE 200 [hp_X]/1 1
INACTIVE INGREDIENTS: LACTOSE; STARCH, POTATO; MAGNESIUM STEARATE

Pleo® Citro TABLETS

PURPOSE

Homeopathic Medicine Citric Acid

Indications

For symptoms of allergies and the common cold.

ACTIVE INGREDIENT

INGREDIENTS

One tablet contains 83.34 mg Acidum citricum 10X, 83.34 mg Acidum citricum 30X, 83.34 mg Acidum citricum 200X in a base of lactose, potato starch, magnesium stearate.

Tamper Evident

Do not use this product if imprinted inner blister pack is broken.

DOSAGE

1-3 × daily 1-2 tablets.

WARNING

ASK DOCTOR

If symptoms persist more than a few days, contact a licensed practitioner.

PREGNANCY OR BREAST FEEDING

As with any drug, if you are pregnant or nursing a baby, seek the advice of a health care professional before using this product.

KEEP OUT OF REACH OF CHILDREN

Keep this and all other medications out of the reach of children. In case of accidental overdose, seek professional assistance or contact a Poison Control Center immediately.

STORAGE AND HANDLING

Protect from light and heat.

Manufactured by: Sanum-Kehlbeck GmbH & Co. KG Hoya, Germany

Distributed by: SANUM USA Corp. 1465 Slater Road Ferndale, WA 98248

PRINCIPAL DISPLAY PANEL - Blister Pack Carton

Pleo® Citro
TABLETS

Homeopathic
Medicine
Citric Acid

The original
SANUM®
brand remedies

Indications: For symptoms of allergies and the common cold.

80 TABLETS